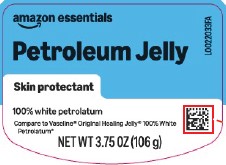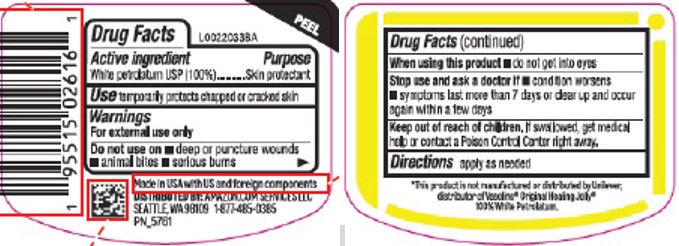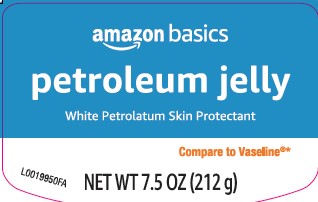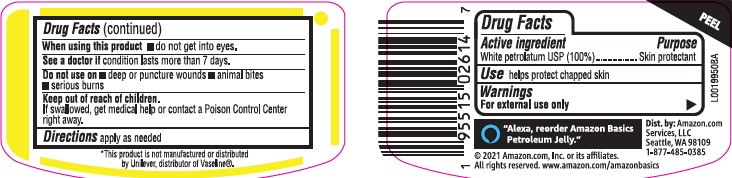 DRUG LABEL: Petroleum
NDC: 72288-069 | Form: JELLY
Manufacturer: Amazon.com Services LLC
Category: otc | Type: HUMAN OTC DRUG LABEL
Date: 20251218

ACTIVE INGREDIENTS: PETROLATUM 1 g/1 g

Essentials_Basics 069.001/069AA
Petroleum Jelly

Active ingredient

White petrolatum USP (100%)

purpose

Skin Protectant

Uses

temporarily protects chapped or cracked skin

Warnings

For external use only

When using this product

- do not get into eyes

Stop use and see a doctor if

- condition worsens
- symptoms last more than 7 days or clear up and occur again within a few days

Do not use on

- deep or puncture wounds
- animal bites
- serious burns

Keep out of reach of children.

If swallowed, get medical help or contact a Poison Control Center right away.

Directions

apply as needed

Inactive ingredients

None

Disclaimer

*This product is not manufactured or distributed by Unilever, distributor of VaselineOriginal Healing Jelly 100% White Petrolatum.

Adverse Reactions

Made in USA with US and foreign components.

DISTRIBUTED BY: Amazon.com Services LLC

Seattle, WA 98109 1-877-485-0385

Principal display panel

amazon essentials

Petroleum Jelly

Skin Protectant

100% white petrolatum

Compare to Vaseline®Original Healing Jelly 100% White Petrolatum*

NET WT 3.75 OZ (106 g)

Principal display panel

amazon basics

petroleum jelly

White Petrolatum Skin Protectant

Compare to Vaseline®*

NET WT 7.5 OZ (212 g)